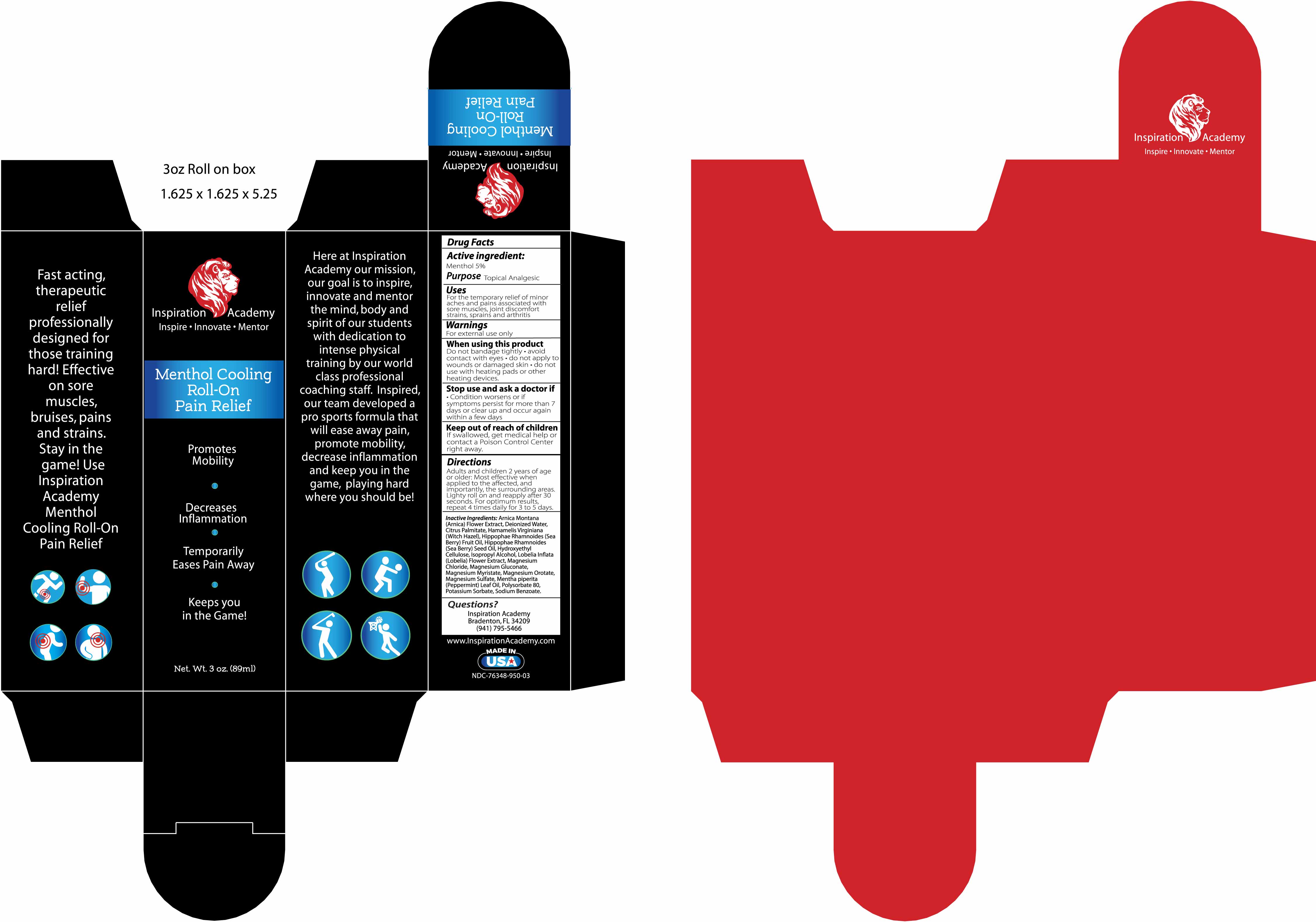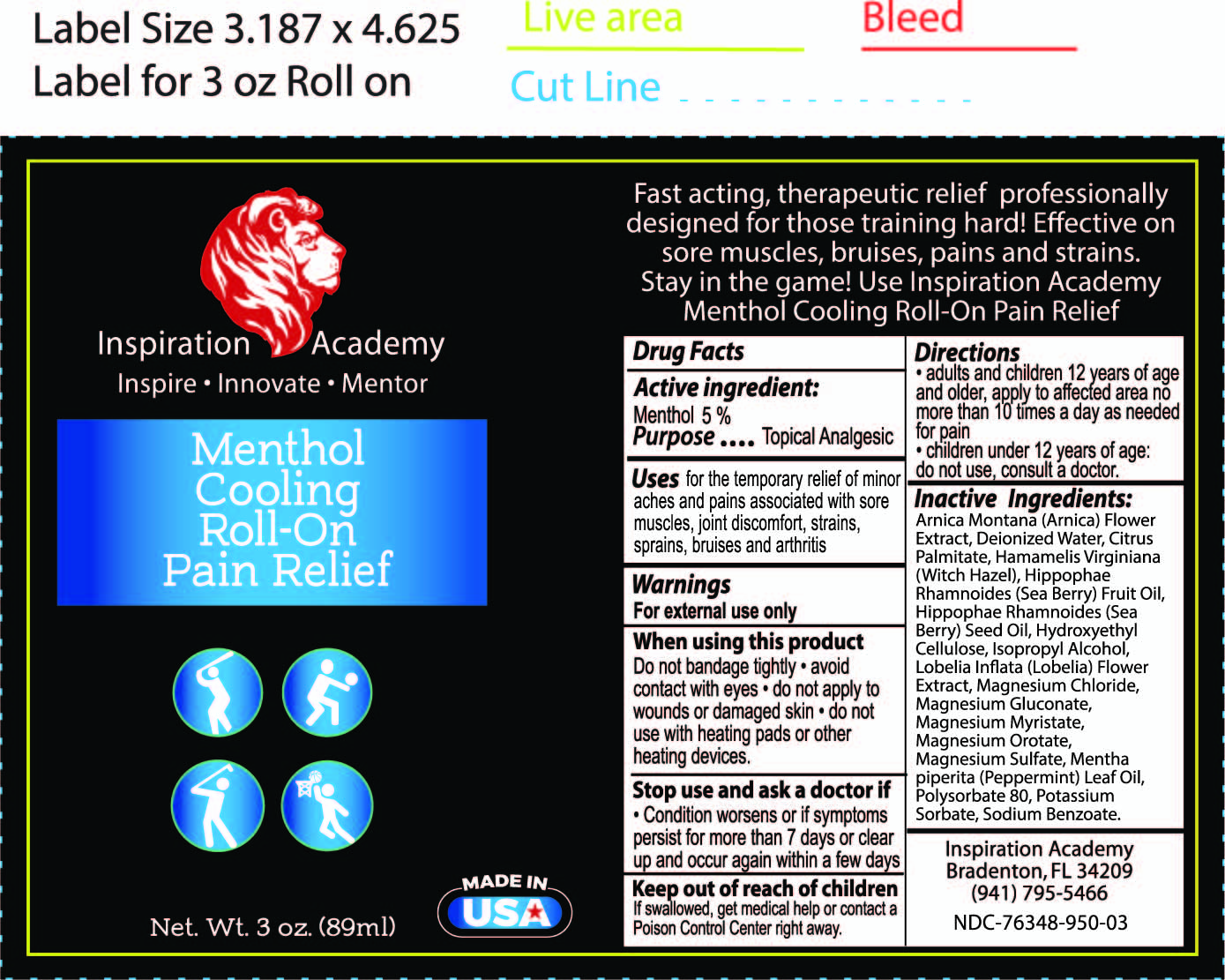 DRUG LABEL: INSPIRATION ACADEMY MENTHOL COOLING ROLL ON
NDC: 76348-950 | Form: LIQUID
Manufacturer: RENU LABORATORIES, INC.
Category: otc | Type: HUMAN OTC DRUG LABEL
Date: 20220114

ACTIVE INGREDIENTS: MENTHOL 4.2 g/84 g
INACTIVE INGREDIENTS: POLYSORBATE 80; METHYLCELLULOSE (4000 CPS); MAGNESIUM SULFATE, UNSPECIFIED; PEPPERMINT OIL; WATER; WITCH HAZEL; MAGNESIUM CHLORIDE; ARNICA MONTANA; SODIUM BENZOATE; POTASSIUM SORBATE; ISOPROPYL ALCOHOL

Inspiration Academy Menthol Cooling Roll-On

Active ingredient

Menthol 5 percent

Purpose

Topical Analgesic

Warnings

For external use only

When using this product

Do not bandage tightly

- avoid contact with eyes
- do not apply to wounds or damaged skin
- do not use with heating pads or other heating devices.

Stop use and ask a doctor if

- Condition worsens or if symptoms persist for more than 7 days or clear up and occur again within a few days.

Keep out of reach of children

If swallowed, get medical help or contact a Poison Control Center right away.

Directions

- adults and children 12 years of age and older, apply to affected area no more than 10 times a day as needed for pain.
- children under 12 years of age: do not use, consulta a doctor.

RECENT MAJOR CHANGES

THERE ARE NO SUBSTANTIVE LABELING CHANGES IN THE SECTION

- dosage and administration

INACTIVE INGREDIENT

Arnica Montana (Arnica) Flower Extract, Cannabis Sativa (Hemp) Seed Oil and Hemp Derived Cannabidiol Extract with proprietary terpene blend (Limonene, Myrcene, Caryophyllene, Linalool, Pinene, Terpineol), Deionized Water, Fragrance, Hamamelis Virginiana (Witch Hazel), Hydroxyethyl Cellulose, Isopropyl Alcohol, Magnesium Chloride, Mentha piperita (Peppermint) Leaf Oil, Polysorbate 80, Potassium Sorbate, Sodium Benzoate.

Questions? Comments?

www.HempforLifeWellness.com

Uses

For the temporary relief of minor aches and pains associated with sore muscles, joint discomfort strains, sprains and arthritis.